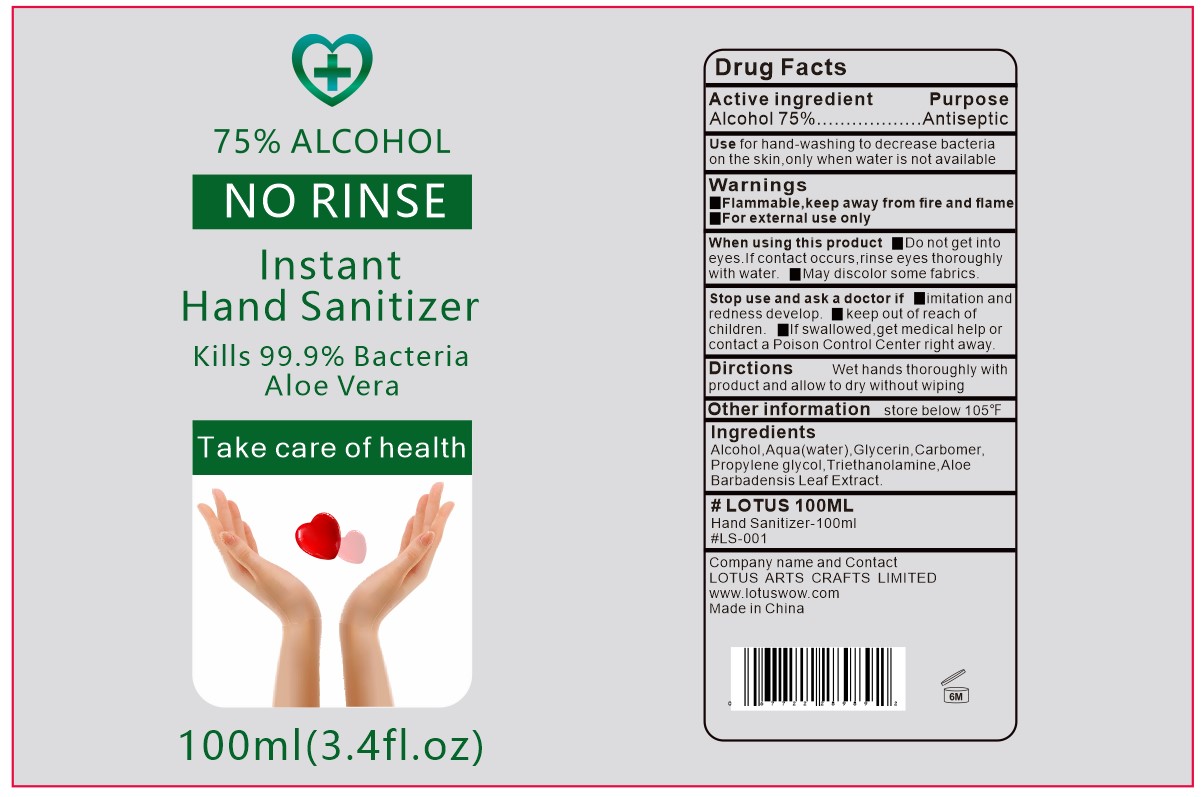 DRUG LABEL: Instant Hand Sanitizer
NDC: 78294-001 | Form: GEL
Manufacturer: LOTUS ARTS CRAFTS LIMITED
Category: otc | Type: HUMAN OTC DRUG LABEL
Date: 20200522

ACTIVE INGREDIENTS: ALCOHOL 75 mL/100 mL
INACTIVE INGREDIENTS: PROPYLENE GLYCOL 0.2 mL/100 mL; GLYCERIN 0.5 mL/100 mL; CARBOMER HOMOPOLYMER, UNSPECIFIED TYPE 0.3 mL/100 mL; WATER 23.55 mL/100 mL; TROLAMINE 0.3 mL/100 mL; ALOE VERA LEAF 0.1 mL/100 mL

hand sanitizer

Active Ingredient(s)

Alcohol 75%

Purpose

Antiseptic

Use for hand

washing to decrease bacteria on the skin ,only when water is not available

Warnings

For external use only. Flammable. Keep away from heat or flame

Do not use

Do not get into eyes. If contact occurs ,rinse eyes thoroughly with water

When using this product keep out of eyes, ears, and mouth. In case of contact with eyes, rinse eyes thoroughly with water.
Stop use and ask a doctor if irritation or rash occurs. These may be signs of a serious condition.
Keep out of reach of children. If swallowed, get medical help or contact a Poison Control Center right away.

STOP USE

Imitation and redness develop.
Keep out of reach of children.
If swallowed ,get medical help for contact a Poison Control Center right away.

Keep out of reach of children.

Directions

Wet hands thoroughly with product and allow to dry without wiping

Other information

Store below 105° F

Inactive ingredients

Aqua(water) ,Glycerin, Carbomer, Propylene glycol, Triethanolamine ,Aloe Barbadensis Leaf Extract